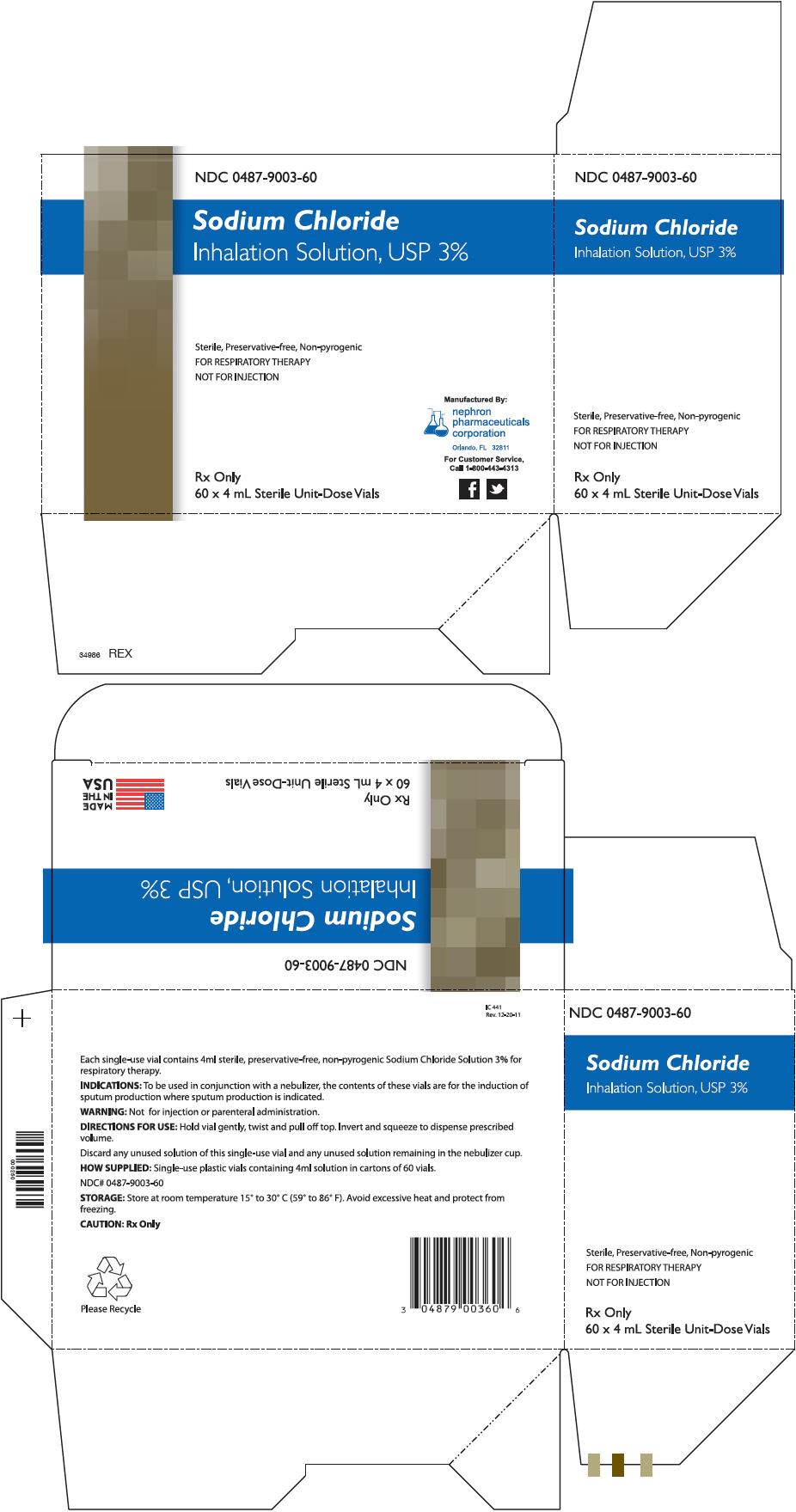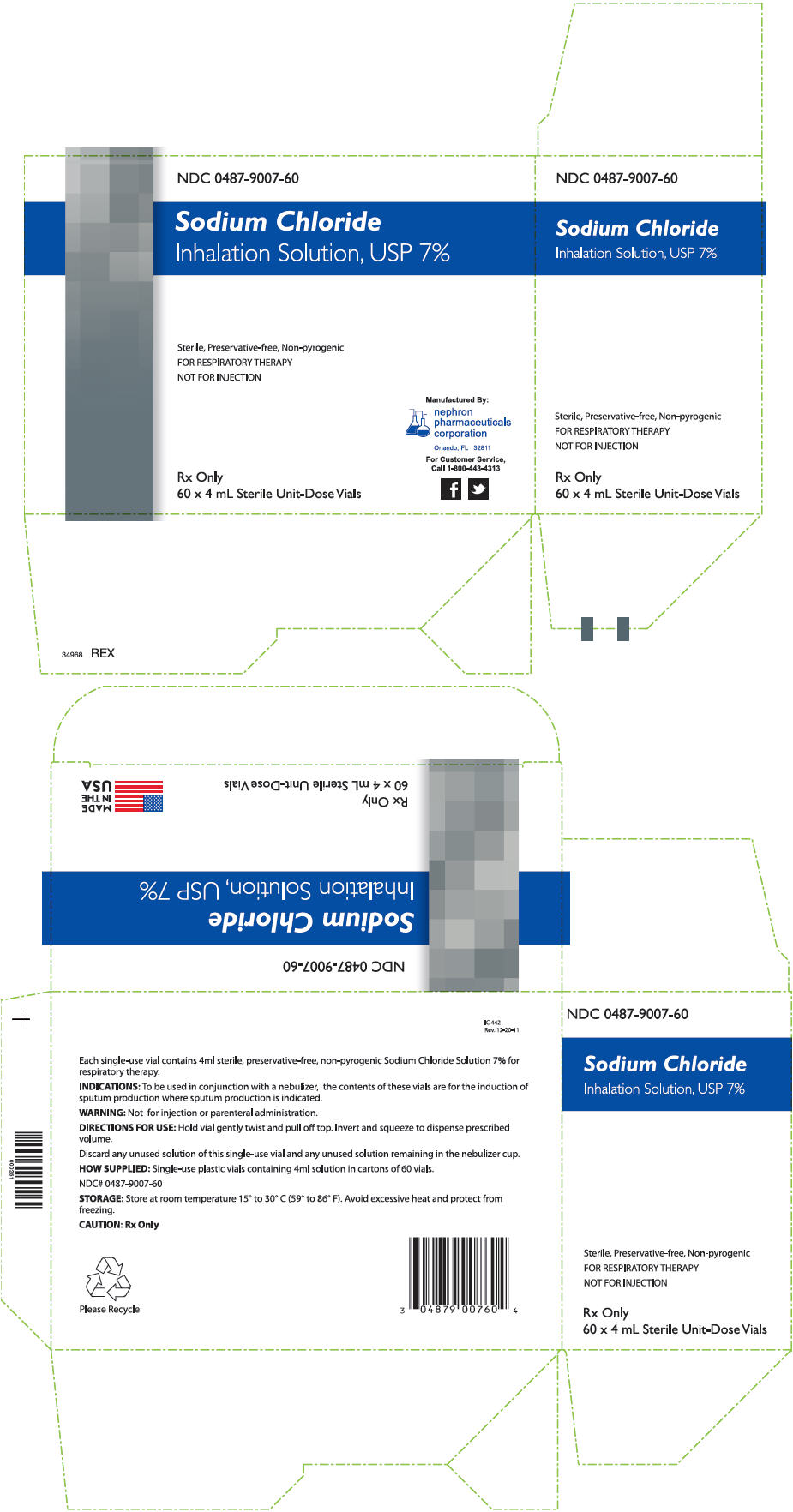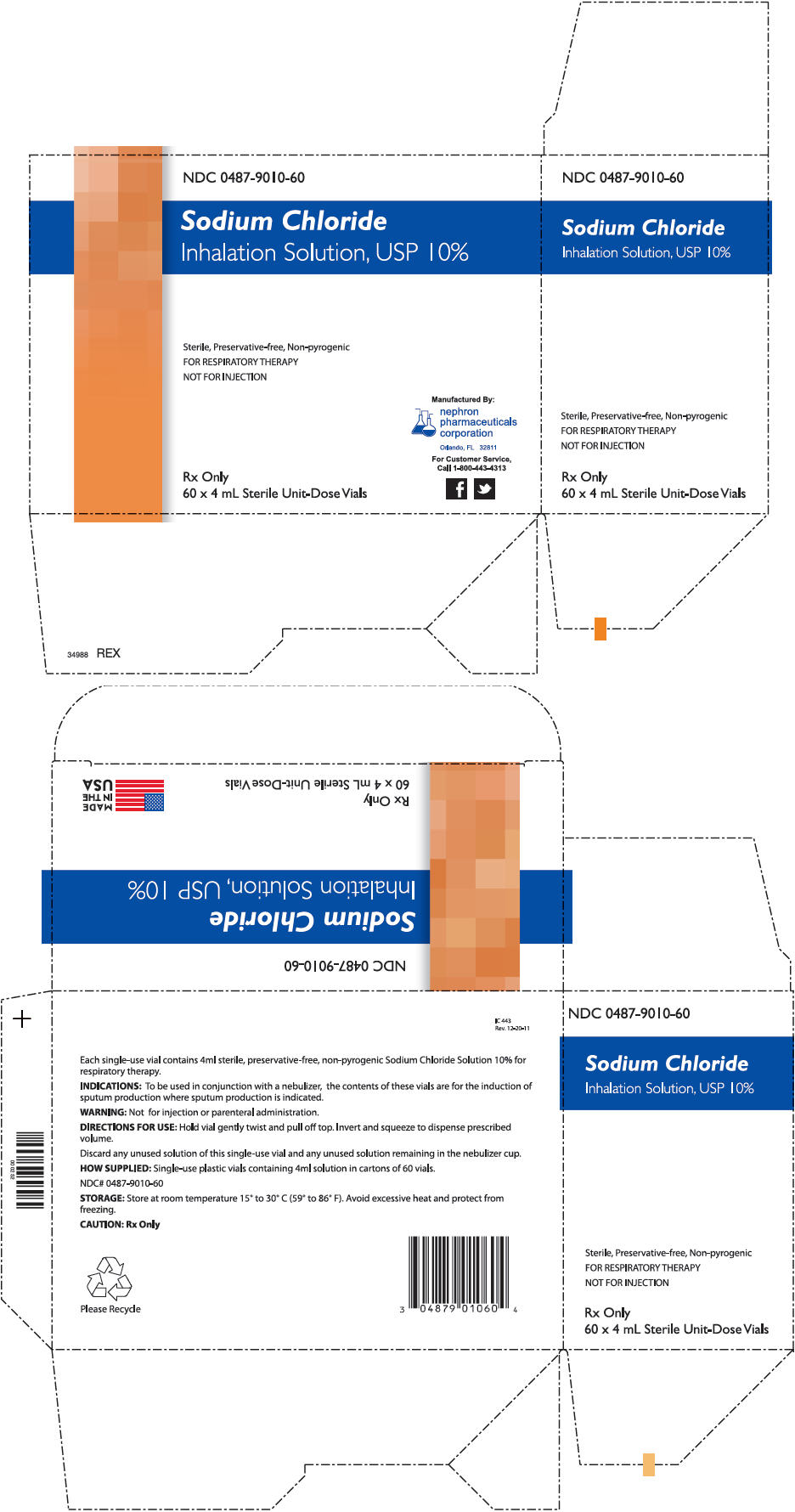 DRUG LABEL: Sodium Chloride
NDC: 0487-9003
Manufacturer: Nephron Pharmaceuticals Corporation
Category: other | Type: MEDICAL DEVICE
Date: 20140917

ACTIVE INGREDIENTS: Sodium Chloride 120 mg/4 mL
INACTIVE INGREDIENTS: Water

Sodium Chloride Inhalation Solution

Sodium Chloride Inhalation Solution, USP 3%

NDC 0487-9003-60

Sodium Chloride
Inhalation Solution, USP 3%

Sterile, Preservative-free, Non-pyrogenic
FOR RESPIRATORY THERAPY
NOT FOR INJECTION

Rx Only
60 x 4 mL Sterile Unit-Dose Vials

Manufactured By:
nephron
pharmaceuticals
corporation
Orlando, FL 32811

For Customer Service,
Call 1-800-443-4313

Each single-use vial contains 4ml sterile, preservative-free, non-pyrogenic Sodium Chloride Solution 3% for respiratory therapy.

INDICATIONS: To be used in conjunction with a nebulizer, the contents of these vials are for the induction of sputum production where sputum production is indicated.

WARNING: Not for injection or parenteral administration.

DIRECTIONS FOR USE: Hold vial gently twist and pull off top. Invert and squeeze to dispense prescribed volume.

Discard any unused solution of this single-use vial and any unused solution remaining in the nebulizer cup.

HOW SUPPLIED: Single-use plastic vials containing 4ml solution in cartons of 60 vials.

NDC# 0487-9003-60

STORAGE: Store at room temperature 15° to 30° C (59° to 86° F). Avoid excessive heat and protect from freezing.

CAUTION: Rx Only

Please Recycle

IC 441
Rev. 12-20-11

Sodium Chloride Inhalation Solution, USP 7%

NDC 0487-9007-60

Sodium Chloride
Inhalation Solution, USP 7%

Sterile, Preservative-free, Non-pyrogenic
FOR RESPIRATORY THERAPY
NOT FOR INJECTION

Rx Only
60 x 4 mL Sterile Unit-Dose Vials

Manufactured By:
nephron
pharmaceuticals
corporation
Orlando, FL 32811

For Customer Service,
Call 1-800-443-4313

Each single-use vial contains 4ml sterile, preservative-free, non-pyrogenic Sodium Chloride Solution 7% for respiratory therapy.

INDICATIONS: To be used in conjunction with a nebulizer, the contents of these vials are for the induction of sputum production where sputum production is indicated.

WARNING: Not for injection or parenteral administration.

DIRECTIONS FOR USE: Hold vial gently twist and pull off top. Invert and squeeze to dispense prescribed volume.

Discard any unused solution of this single-use vial and any unused solution remaining in the nebulizer cup.

HOW SUPPLIED: Single-use plastic vials containing 4ml solution in cartons of 60 vials.

NDC# 0487-9007-60

STORAGE: Store at room temperature 15° to 30° C (59° to 86° F). Avoid excessive heat and protect from freezing.

CAUTION: Rx Only

Please Recycle

IC 442
Rev. 12-20-11

Sodium Chloride Inhalation Solution, USP 10%

NDC 0487-9010-60

Sodium Chloride
Inhalation Solution, USP 10%

Sterile, Preservative-free, Non-pyrogenic
FOR RESPIRATORY THERAPY
NOT FOR INJECTION

Rx Only
60 x 4 mL Sterile Unit-Dose Vials

Manufactured By:
nephron
pharmaceuticals
corporation
Orlando, FL 32811

For Customer Service,
Call 1-800-443-4313

Each single-use vial contains 4ml sterile, preservative-free, non-pyrogenic Sodium Chloride Solution 10% for respiratory therapy.

INDICATIONS: To be used in conjunction with a nebulizer, the contents of these vials are for the induction of sputum production where sputum production is indicated.

WARNING: Not for injection or parenteral administration.

DIRECTIONS FOR USE: Hold vial gently twist and pull off top. Invert and squeeze to dispense prescribed volume.

Discard any unused solution of this single-use vial and any unused solution remaining in the nebulizer cup.

HOW SUPPLIED: Single-use plastic vials containing 4ml solution in cartons of 60 vials.

NDC# 0487-9010-60

STORAGE: Store at room temperature 15° to 30° C (59° to 86° F). Avoid excessive heat and protect from freezing.

CAUTION: Rx Only

Please Recycle

IC 443
Rev. 12-20-11